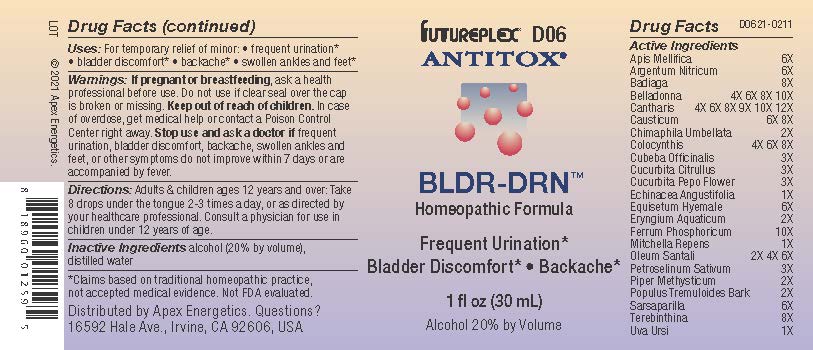 DRUG LABEL: D06
NDC: 63479-0406 | Form: SOLUTION/ DROPS
Manufacturer: Apex Energetics Inc.
Category: homeopathic | Type: HUMAN OTC DRUG LABEL
Date: 20240108

ACTIVE INGREDIENTS: SANDALWOOD OIL 6 [hp_X]/1 mL; PETROSELINUM CRISPUM 3 [hp_X]/1 mL; CHIMAPHILA UMBELLATA 2 [hp_X]/1 mL; SILVER NITRATE 6 [hp_X]/1 mL; SPONGILLA LACUSTRIS 8 [hp_X]/1 mL; FERROSOFERRIC PHOSPHATE 10 [hp_X]/1 mL; TURPENTINE OIL 8 [hp_X]/1 mL; SMILAX ORNATA ROOT 6 [hp_X]/1 mL; LYTTA VESICATORIA 12 [hp_X]/1 mL; CAUSTICUM 8 [hp_X]/1 mL; CITRULLUS COLOCYNTHIS FRUIT PULP 8 [hp_X]/1 mL; WATERMELON SEED 3 [hp_X]/1 mL; CUCURBITA PEPO FLOWER 3 [hp_X]/1 mL; POPULUS TREMULOIDES BARK 2 [hp_X]/1 mL; ARCTOSTAPHYLOS UVA-URSI LEAF 1 [hp_X]/1 mL; ATROPA BELLADONNA 10 [hp_X]/1 mL; PIPER CUBEBA FRUIT 3 [hp_X]/1 mL; ECHINACEA ANGUSTIFOLIA 1 [hp_X]/1 mL; EQUISETUM HYEMALE 6 [hp_X]/1 mL; MITCHELLA REPENS 1 [hp_X]/1 mL; ERYNGIUM YUCCIFOLIUM ROOT 2 [hp_X]/1 mL; MACROPIPER METHYSTICUM ROOT 2 [hp_X]/1 mL; APIS MELLIFERA 6 [hp_X]/1 mL
INACTIVE INGREDIENTS: ALCOHOL; WATER

D06

Active Ingredients
Apis Mellifica | 6X
Argentum Nitricum | 6X
Badiaga | 8X
Belladonna | 4X 6X 8X 10X
Cantharis | 4X 6X 8X 9X 10X 12X
Causticum | 6X 8X
Chimaphila Umbellata | 2X
Colocynthis | 4X 6X 8X
Cubeba Officinalis | 3X
Cucurbita Citrullus | 3X
Cucurbita Pepo Flower | 3X
Echinacea Angustifolia | 1X
Equisetum Hyemale | 6X
Eryngium Aquaticum | 2X
Ferrum Phosphoricum | 10X
Mitchella Repens | 1X
Oleum Santali | 2X 4X 6X
Petroselinum Sativum | 3X
Piper Methysticum | 2X
Populus Tremuloides Bark | 2X
Sarsaparilla | 6X
Terebinthina | 8X
Uva Ursi | 1X

INDICATIONS AND USAGE

Uses:

For temporary relief of minor:

frequent urination*

bladder discomfort*

backache*

swollen ankles and feet*

*Claims based on traditional homeopathic practice, not accepted medical evidence. Not FDA evaluated.

Warnings:

PREGNANCY OR BREAST FEEDING

If pregnant or breastfeeding, ask a health professional before use.

Do not use if clear seal over the cap is broken or missing.

Keep out of reach of children. In case of overdose, get medical help or contact a Poison Control Center right away.

Stop use and ask a doctor if frequent urination, bladder discomfort, backache, swollen ankles and feet, or other symptoms do not improve within 7 days or are accompanied by fever.

Directions:

Adults & children ages 12 years and over: Take 8 drops under the tongue 2-3 times a day, or as directed by your healthcare professional. Consult a physician for use in children under 12 years of age.

Inactive Ingredients

alcohol (20% by volume), distilled water

Distributed by Apex Energetics. Questions?

16592 Hale Ave., Irvine, CA 92606, USA

PACKAGE LABEL

FUTUREPLEX® D06

ANTITOX®

BLDR-DRN™

Homeopathic Formula

Frequent Urination*

Bladder Discomfort*

Backache*

1 fl oz (30 mL)

Alcohol 20% by Volume